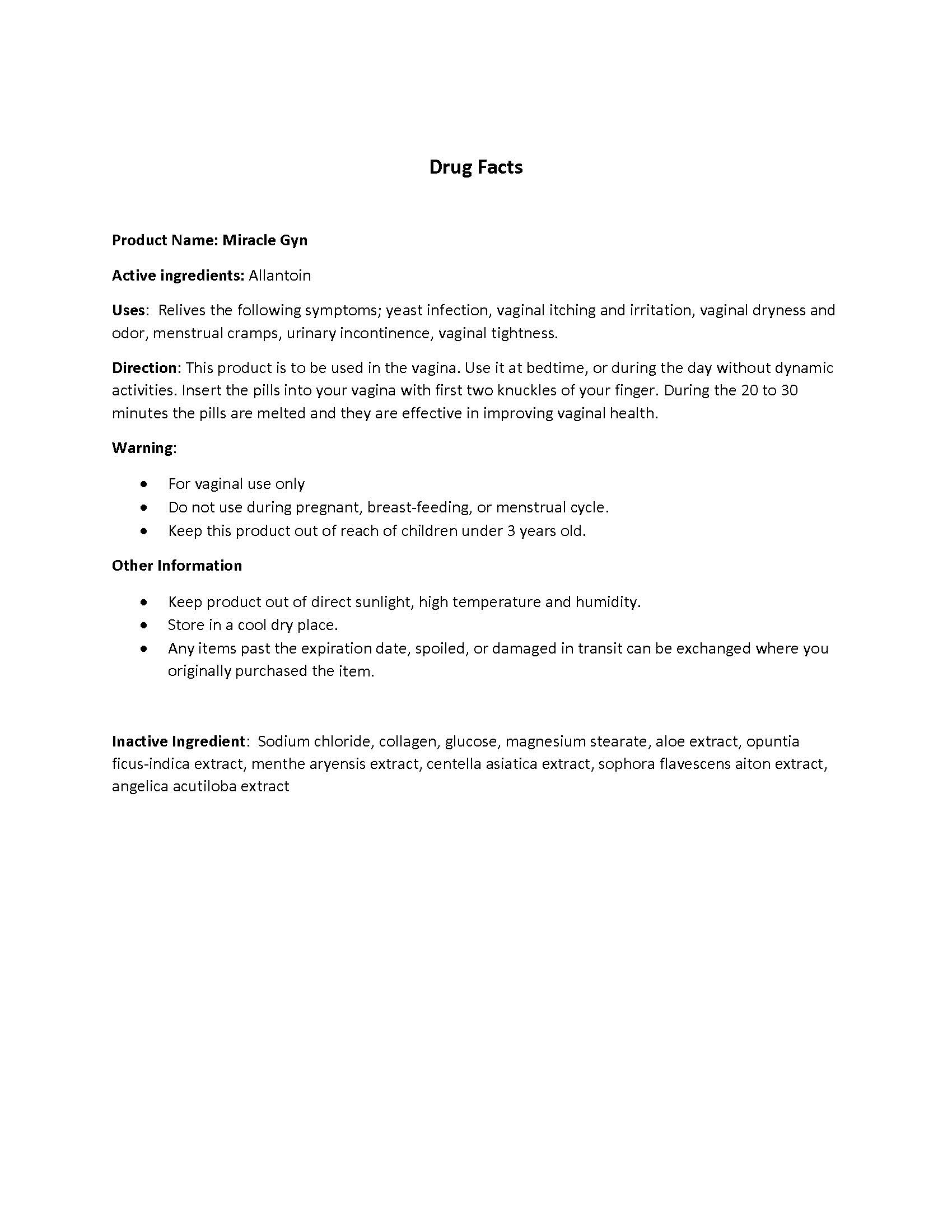 DRUG LABEL: MIRACLE GYN
NDC: 55618-2001 | Form: TABLET
Manufacturer: HA U DONG CHUN
Category: otc | Type: HUMAN OTC DRUG LABEL
Date: 20150627

ACTIVE INGREDIENTS: ALLANTOIN 0.2 1/1 1
INACTIVE INGREDIENTS: SODIUM CHLORIDE; COLLAGENASE CLOSTRIDIUM HISTOLYTICUM; DEXTROSE; MAGNESIUM STEARATE; ALOE; OPUNTIA FICUS-INDICA; MENTHA ARVENSIS FLOWER OIL; CENTELLA ASIATICA; SOPHORA FLAVESCENS ROOT; ANGELICA ACUTILOBA ROOT OIL

ACTIVE INGREDIENT

Allantoin

PURPOSE

Relives the following symptoms; yeast infection, vaginal itching and irritation, vaginal dryness and odor, menstrual cramps, urinary incontinence, vaginal tightness.

KEEP OUT OF REACH OF CHILDREN

INDICATIONS & USAGE

This product is to be used in the vagina. Use it at bedtime, or during the day without dynamic activities. Insert the pills into your vagina with first two knuckles of your finger. During the 20 to 30 minutes the pills are melted and they are effective in improving vaginal health.

WARNINGS

- Do not use during pregnant, breast-feeding, or menstrual cycle.
- Keep this product out of reach of children under 3 years old.

DOSAGE & ADMINISTRATION

For vaginal use only.

OTHER SAFETY INFORMATION

- Keep product out of direct sunlight, high temperature and humidity.
- Store in a cool dry place.
- Any items past the expiration date, spoiled, or damaged in transit can be exchanged where you originally purchased the item.

INACTIVE INGREDIENT

Sodium chloride, collagen, glucose, magnesium stearate, aloe extract, opuntia ficus-indica extract, menthe aryensis extract, centella asiatica extract, sophora flavescens aiton extract, angelica acutiloba extract